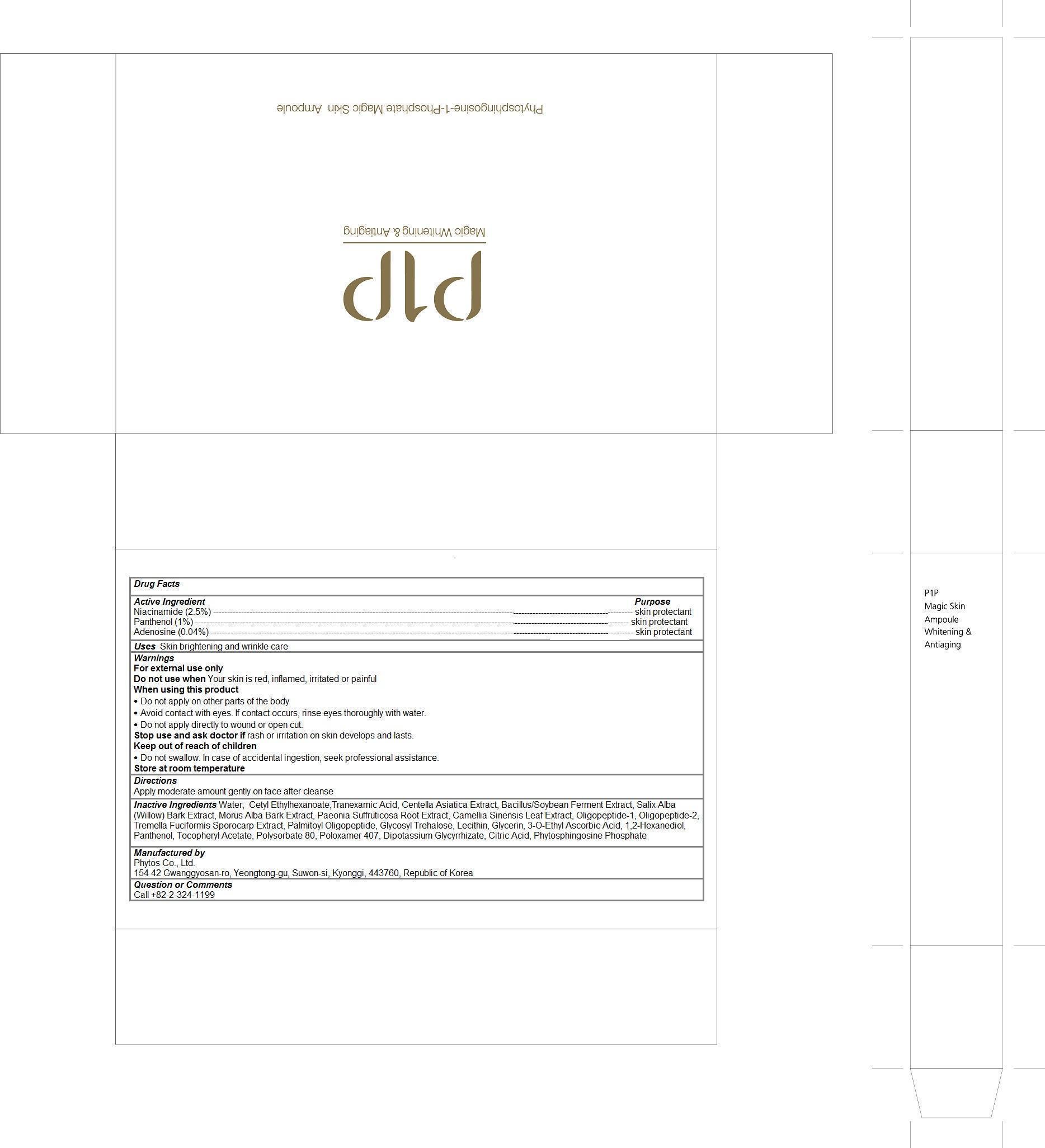 DRUG LABEL: P1P Magic Whitening Antiaging
NDC: 69579-104 | Form: LIQUID
Manufacturer: Phytos Co., Ltd.
Category: otc | Type: HUMAN OTC DRUG LABEL
Date: 20150218

ACTIVE INGREDIENTS: niacinamide 0.025 1/5 mL; PANTHENOL 0.01 1/5 mL; adenosine 0.0004 1/5 mL
INACTIVE INGREDIENTS: water; CETYL ETHYLHEXANOATE; TRANEXAMIC ACID; CENTELLA ASIATICA; SALIX ALBA BARK; morus alba bark; PAEONIA SUFFRUTICOSA ROOT; GREEN TEA LEAF; PALMITOYL OLIGOPEPTIDE; EGG PHOSPHOLIPIDS; glycerin; 3-O-ETHYL ASCORBIC ACID; 1,2-HEXANEDIOL; .ALPHA.-TOCOPHEROL ACETATE; POLYSORBATE 80; POLOXAMER 407; GLYCYRRHIZINATE DIPOTASSIUM; CITRIC ACID MONOHYDRATE

P1P Magic Whitening & Antiaging